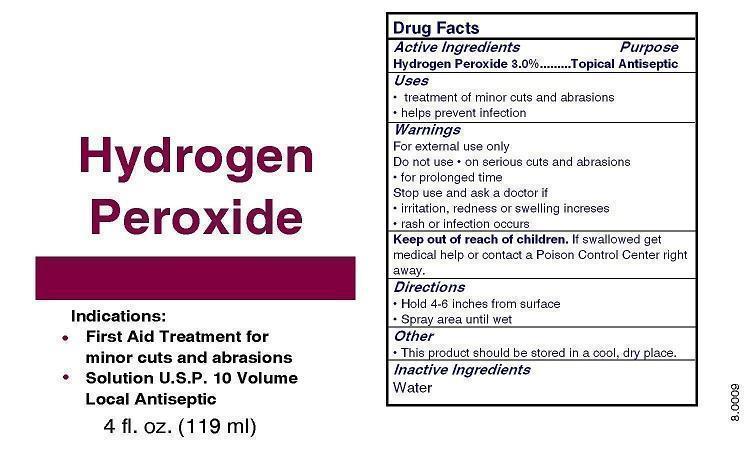 DRUG LABEL: Your Label Here Hydrogen Peroxide First Aid
NDC: 52982-124 | Form: SPRAY, METERED
Manufacturer: Dixon Investments, Inc.
Category: otc | Type: HUMAN OTC DRUG LABEL
Date: 20130408

ACTIVE INGREDIENTS: HYDROGEN PEROXIDE 3.57 mL/119 mL
INACTIVE INGREDIENTS: WATER

YOUR LABEL HERE HYDROGEN PEROXIDE PUMP SPRAY

Active Ingredients

Hydrogen Peroxide 3.0%

Purpose

Topical Antiseptic

Uses

treatment of minor cuts and abrasions
help prevent infection

Warnings

For external use only

Do not use

on serious cuts and abrasions
for prolonged time

Stop use and ask a doctor if

irritation, redness or swelling increases
rash or infection occurs

Keep out of reach of children.

If swallowed get medical help or contact a Poison Control Center right away.

Directions

Hold 4-6 inches from surface
Spray area until wet

Other

This product should be stored in a cool, dry place.

Inactive Ingredients

Water